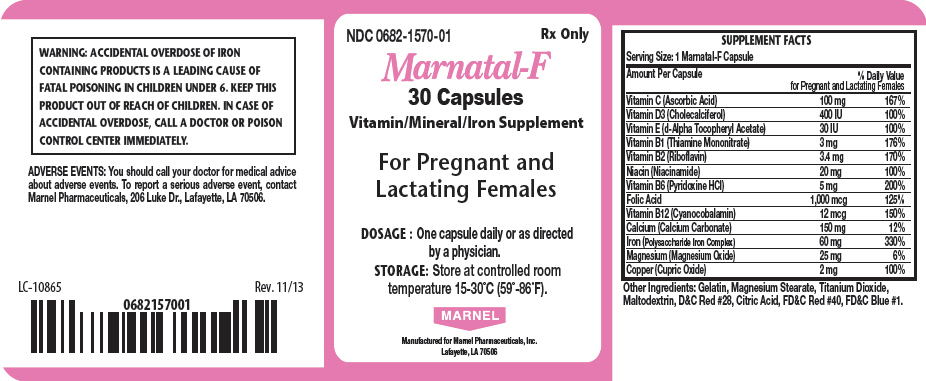 DRUG LABEL: Marnatal F
NDC: 0682-1570 | Form: CAPSULE
Manufacturer: Marnel Pharmaceuticals, Inc.
Category: prescription | Type: HUMAN PRESCRIPTION DRUG LABEL
Date: 20140506

ACTIVE INGREDIENTS: ASCORBIC ACID 100 mg/1 1; CHOLECALCIFEROL 400 [iU]/1 1; .ALPHA.-TOCOPHEROL ACETATE, D- 30 [iU]/1 1; THIAMINE MONONITRATE 3 mg/1 1; RIBOFLAVIN 3.4 mg/1 1; NIACINAMIDE 20 mg/1 1; PYRIDOXINE HYDROCHLORIDE 5 mg/1 1; FOLIC ACID 1000 ug/1 1; CYANOCOBALAMIN 12 ug/1 1; CALCIUM CARBONATE 150 mg/1 1; IRON SUCROSE 60 mg/1 1; MAGNESIUM OXIDE 25 mg/1 1; CUPRIC OXIDE 2 mg/1 1
INACTIVE INGREDIENTS: GELATIN; MAGNESIUM STEARATE; TITANIUM DIOXIDE; MALTODEXTRIN; D&C RED NO. 28; CITRIC ACID MONOHYDRATE; FD&C RED NO. 40; FD&C BLUE NO. 1

Marnatal-F

WARNING

ACCIDENTAL OVERDOSE OF IRON CONTAINING PRODUCTS IS A LEADING CAUSE OF FATAL POISONING IN CHILDREN UNDER 6. KEEP THIS PRODUCT OUT OF REACH OF CHILDREN. IN CASE OF ACCIDENTAL OVERDOSE, CALL A DOCTOR OR POISON CONTROL CENTER IMMEDIATELY.

ADVERSE EVENTS

You should call your doctor for medical advice about adverse events. To report a serious adverse event, contact Marnel Pharmaceuticals, 206 Luke Dr., Lafayette, LA 70506.

SUPPLEMENT FACTS
Serving Size: 1 Marnatal-F Capsule
Amount Per Capsule | % Daily Value for Pregnant and Lactating Females
Vitamin C (Ascorbic Acid) | 100 mg | 167%
Vitamin D3 (Cholecalciferol) | 400 IU | 100%
Vitamin E (d-Alpha Tocopheryl Acetate) | 30 IU | 100%
Vitamin B1 (Thiamine Mononitrate) | 3 mg | 176%
Vitamin B2 (Riboflavin) | 3.4 mg | 170%
Niacin (Niacinamide) | 20 mg | 100%
Vitamin B6 (Pyridoxine HCl) | 5 mg | 200%
Folic Acid | 1,000 mcg | 125%
Vitamin B12 (Cyanocobalamin) | 12 mcg | 150%
Calcium (Calcium Carbonate) | 150 mg | 12%
Iron (Polysaccharide Iron Complex) | 60 mg | 330%
Magnesium (Magnesium Oxide) | 25 mg | 6%
Copper (Cupric Oxide) | 2 mg | 100%

Other Ingredients

Gelatin, Magnesium Stearate, Titanium Dioxide, Maltodextrin, D&C Red #28, Citric Acid, FD&C Red #40, FD&C Blue #1.

LC-10865
Rev. 11/13

PRINCIPAL DISPLAY PANEL - 30 Capsule Bottle Label

NDC 0682-1570-01
Rx Only

Marnatal-F
30 Capsules
Vitamin/Mineral/Iron Supplement

For Pregnant and
Lactating Females

DOSAGE : One capsule daily or as directed
by a physician.
STORAGE: Store at controlled room
temperature 15-30°C (59°-86°F).

MARNEL

Manufactured for Marnel Pharmaceuticals, Inc.
Lafayette, LA 70506